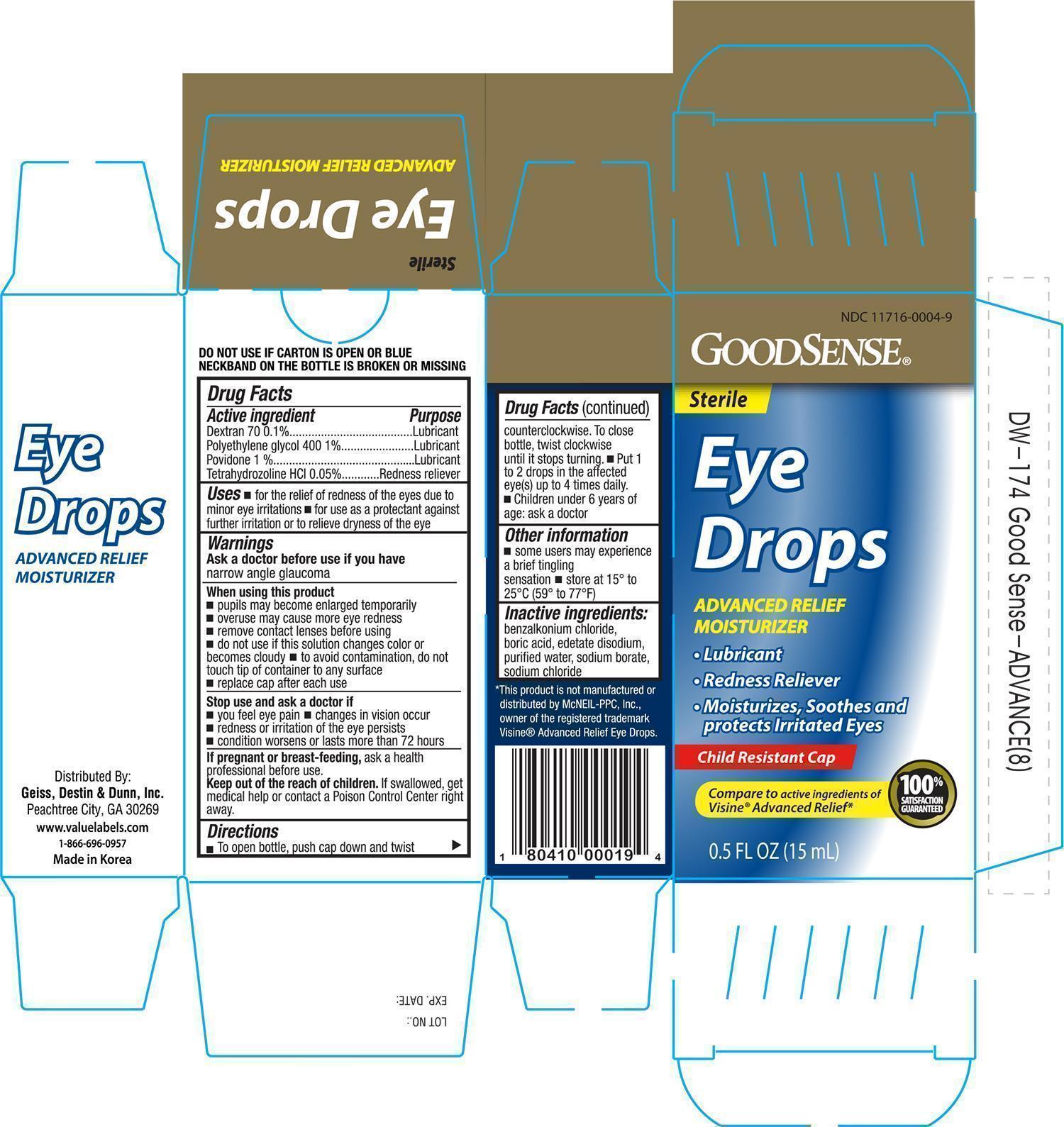 DRUG LABEL: GOODSENSE ADVANCED RELIEF EYE
NDC: 11716-0004 | Form: SOLUTION/ DROPS
Manufacturer: HANLIM PHARM. CO., LTD.
Category: otc | Type: HUMAN OTC DRUG LABEL
Date: 20141219

ACTIVE INGREDIENTS: DEXTRAN 70 1 mg/1 mL; POLYETHYLENE GLYCOL 400 10 mg/1 mL; POVIDONE 10 mg/1 mL; TETRAHYDROZOLINE HYDROCHLORIDE .5 mg/1 mL
INACTIVE INGREDIENTS: BENZALKONIUM CHLORIDE; BORIC ACID; EDETATE DISODIUM; WATER; SODIUM CHLORIDE; SODIUM BORATE

Active ingredients Purpose

Dextran 70 0.1% .................................................................. Lubricant

Polyethylene glycol 400 1% .................................................... Lubricant

Povidone 1% ........................................................................ Lubricant

Tetrahydrozoline HCL 0.05% .................................................. Redness Reliever

Uses

- for the relief of redness of the eyes due to minor eye irritations
- for use as a protectant against further irritation or to relieve dryness of the eye

Warnings

Ask a doctor before use if you have narrow angle glaucoma

When using this product

- pupils may become enlarged temporarily
- overuse may cause more eye redness
- remove contact lenses before using
- do not use if this solution changes color or becomes cloudy
- to avoid contamination, do not touch tip of container to any surface
- replace cap after each use

Stop use and ask a doctor if

- you feel eye pain
- changes in vision occur
- redness or irritation of the eye lasts
- condition worsens or lasts more than 72 hours

PREGNANCY OR BREAST FEEDING

If pregnant or breast-feeding, ask a health professional before use.

Keep out of the reach of children.

If swallowed, get medical help or contact a Poison Control Center right away.

Directions

- to open bottle, push cap down and twist counterclockwise. To close bottle, twist clockwise until it stops turning
- put 1 to 2 drops in the affected eye(s) up to 4 times daily
- children under 6 years of age: ask a doctor

Other information

- some users may experience a brief tingling
- store at 15o to 25oC (59o to 77oF)

Inactive ingredients:

benzalkonium chloride, boric acid, edetate disodium, purified water, sodium chloride, and sodium borate

DOSAGE AND ADMINISTRATION

Distributed By:

Geiss, Destin & Dunn, Inc.

Peachtree City, GA 30269

www.valuelabels.com

1-866-696-0957

Made in Korea